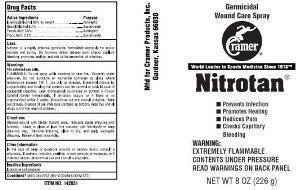 DRUG LABEL: Nitrotan
NDC: 11960-0049 | Form: AEROSOL, SPRAY
Manufacturer: Cramer Products Inc
Category: otc | Type: HUMAN OTC DRUG LABEL
Date: 20130726

ACTIVE INGREDIENTS: ISOPROPYL ALCOHOL 0.62 g/1 g; BENZYL ALCOHOL 0.061 g/1 g; PICRIC ACID 0.002 g/1 g; TANNIC ACID 0.015 g/1 g
INACTIVE INGREDIENTS: ISOBUTANE; PROPANE

Active Ingredients Purpose

Isopropyl alcohol 62% by weight Antiseptic

Benzyl Alcohol 6.1% Bacteriacide

Tannic Acid 1.5% Astringent

Picric Acid 0.2% Bacteriacide

Uses

Nitrotan is a highly effective germicide, formulated expressly for minor wounds and burns. Its four-way action reduces pain, checks capillary bleeding, promotes healing, and aids in the prevention of infection.

Warnings

For external use only.
FLAMMABLE. Do not spray while smoking or near fire. Contents under pressure. Do not puncture or incinerate container or place where temperature exceeds 120 F. Use only as directed. Intentional misuse by concentrating and inhaling the contents can be harmful or fatal. In case of accidental ingestion, seek professional assistance or contact a Poison Control Center immediately. If irritation occurs or if there is no improvement within 2 weeks, discontinue use and consult a doctor. Keep this and all drugs out of the reach of children.

Directions

Cleanse wound with Cinder Suds® soap. Saturate sterile dressing with Nitrotan. Leave in place at least five minutes; add Nitrotan® to keep dressing wet. Remove dressing, allow to dry, and apply antiseptic dressing. Renew at least once daily.

Inactive Ingredients

Isobutane and propane

QUESTIONS

Mfd. by Cramer Products, Inc. Gardner, Kansas 66030

QUESTIONS? (800) 345-2231 (M-F 8:00AM-5:00PM CST)

Purpose

Antiseptic

Bacteriacide

Astringent

Bacteriacide

KEEP OUT OF REACH OF CHILDREN

Keep this and all drugs out of the reach of children.

PACKAGE LABEL

Germicidal Wound Care Spray

Prevents Infection

Promotes Healing

Reduces Pain

Checks Capillary Bleeding

WARNING:

EXTREMELY FLAMMABLE

CONTENTS UNDER PRESSURE

READ WARNINGS ON BACK PANEL

NET WT 8 OZ (226 g)